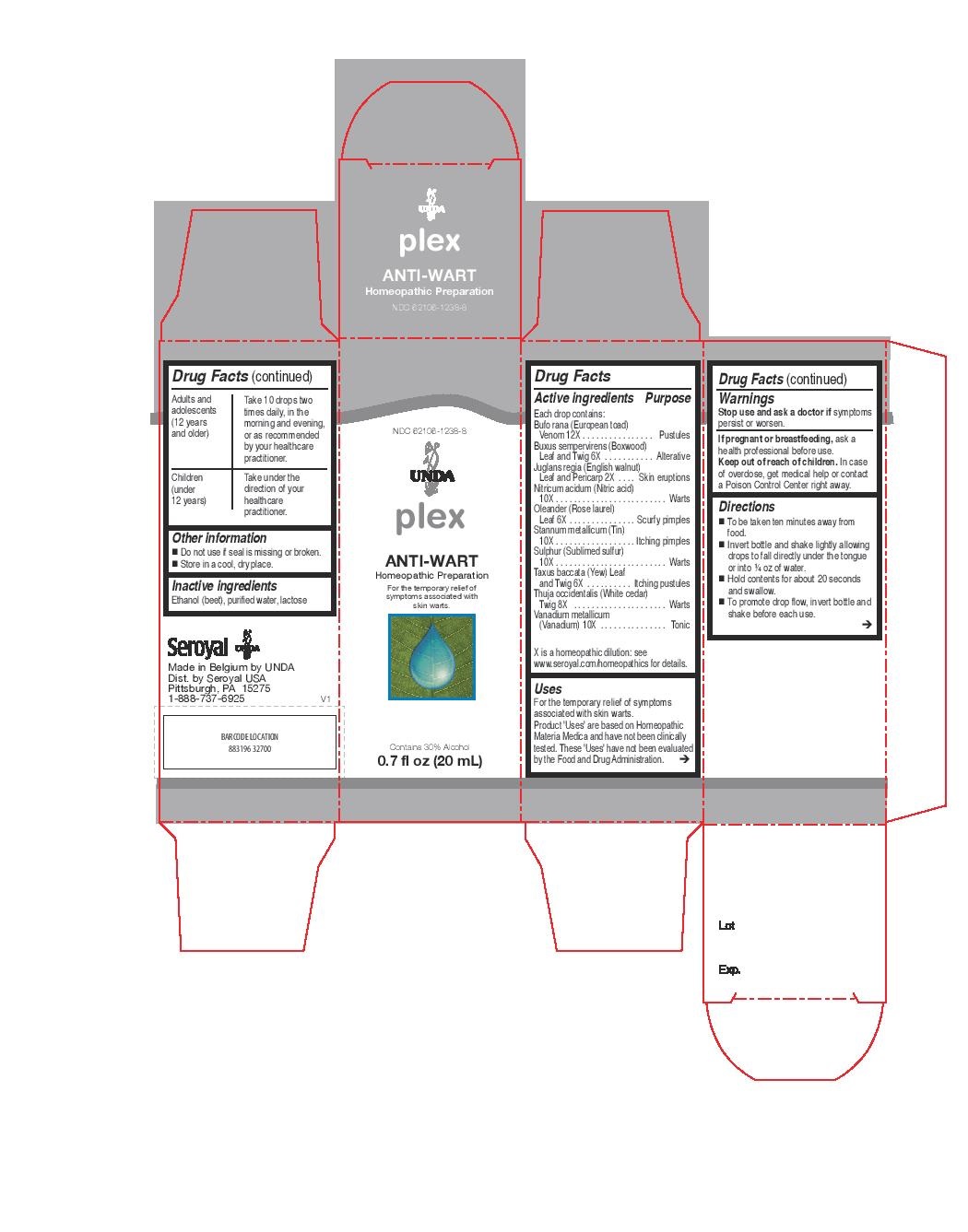 DRUG LABEL: ANTI-WART
NDC: 62106-1238 | Form: LIQUID
Manufacturer: Seroyal USA
Category: homeopathic | Type: HUMAN OTC DRUG LABEL
Date: 20221109

ACTIVE INGREDIENTS: TIN 10 [hp_X]/20 mL; ENGLISH WALNUT 2 [hp_X]/20 mL; NERIUM OLEANDER LEAF 6 [hp_X]/20 mL; BUFO BUFO CUTANEOUS GLAND 12 [hp_X]/20 mL; NITRIC ACID 10 [hp_X]/20 mL; SULFUR 10 [hp_X]/20 mL; THUJA OCCIDENTALIS LEAFY TWIG 8 [hp_X]/20 mL; VANADIUM 10 [hp_X]/20 mL; BUXUS SEMPERVIRENS LEAFY TWIG 6 [hp_X]/20 mL; TAXUS BACCATA WHOLE 6 [hp_X]/20 mL
INACTIVE INGREDIENTS: ALCOHOL; WATER; LACTOSE

ANTI-WART

Active ingredients
Each drop contains:
Bufo rana (European toad) Venom 12X
Buxus sempervirens (Boxwood) Leaf and Twig 6X
Juglans regia (English walnut) Leaf and Pericarp 2X
Nitricum acidum (Nitric acid) 10X
Oleander (Rose laurel) Leaf 6X
Stannum metallicum (Tin) 10X
Sulphur (Sublimed sulfur) 10X
Taxus baccata (Yew) Leaf and Twig 6X
Thuja occidentalis (White cedar) Twig 8X
Vanadium metallicum (Vanadium) 10X

Uses
For the temporary relief of symptoms associated with skin warts.

Warnings
Stop use and ask a doctor if symptoms
persist or worsen.
If pregnant or breastfeeding, ask a
health professional before use.
Keep out of reach of children. In case
of overdose, get medical help or contact
a Poison Control Center right away.

Keep out of reach of children. In case
of overdose, get medical help or contact
a Poison Control Center right away.

PREGNANCY OR BREAST FEEDING

If pregnant or breastfeeding, ask a
health professional before use.

Other information
Do not use if seal is missing or broken.
Store in a cool, dry place.

Inactive ingredients
Ethanol (beet), purified water, lactose

Directions
To be taken ten minutes away from
food.
Invert bottle and shake lightly allowing
drops to fall directly under the tongue
or into ¼ oz of water.
Hold contents for about 20 seconds
and swallow.
To promote drop flow, invert bottle and
shake before each use.

Adults and adolescents (12 years and older)
Take 10 drops two times daily, in the
morning and evening, or as recommended
by your healthcare practitioner.

Children (under 12 years)

Take under the direction of your
healthcare practitioner.

Uses
For the temporary relief of symptoms associated with skin warts.

Directions
To be taken ten minutes away from
food.
Invert bottle and shake lightly allowing
drops to fall directly under the tongue
or into ¼ oz of water.
Hold contents for about 20 seconds
and swallow.
To promote drop flow, invert bottle and
shake before each use.

Adults and adolescents (12 years and older)
Take 10 drops two times daily, in the
morning and evening, or as recommended
by your healthcare practitioner.

Children (under 12 years)

Take under the direction of your
healthcare practitioner.

PACKAGE LABEL

NDC 62106-1238-8

UNDA

plex

ANTI-WART

Homeopathic Preparation

For the temporary relief of symptoms associated with skin warts.

Contains 30% Alcohol

0.7 fl oz (20 mL)